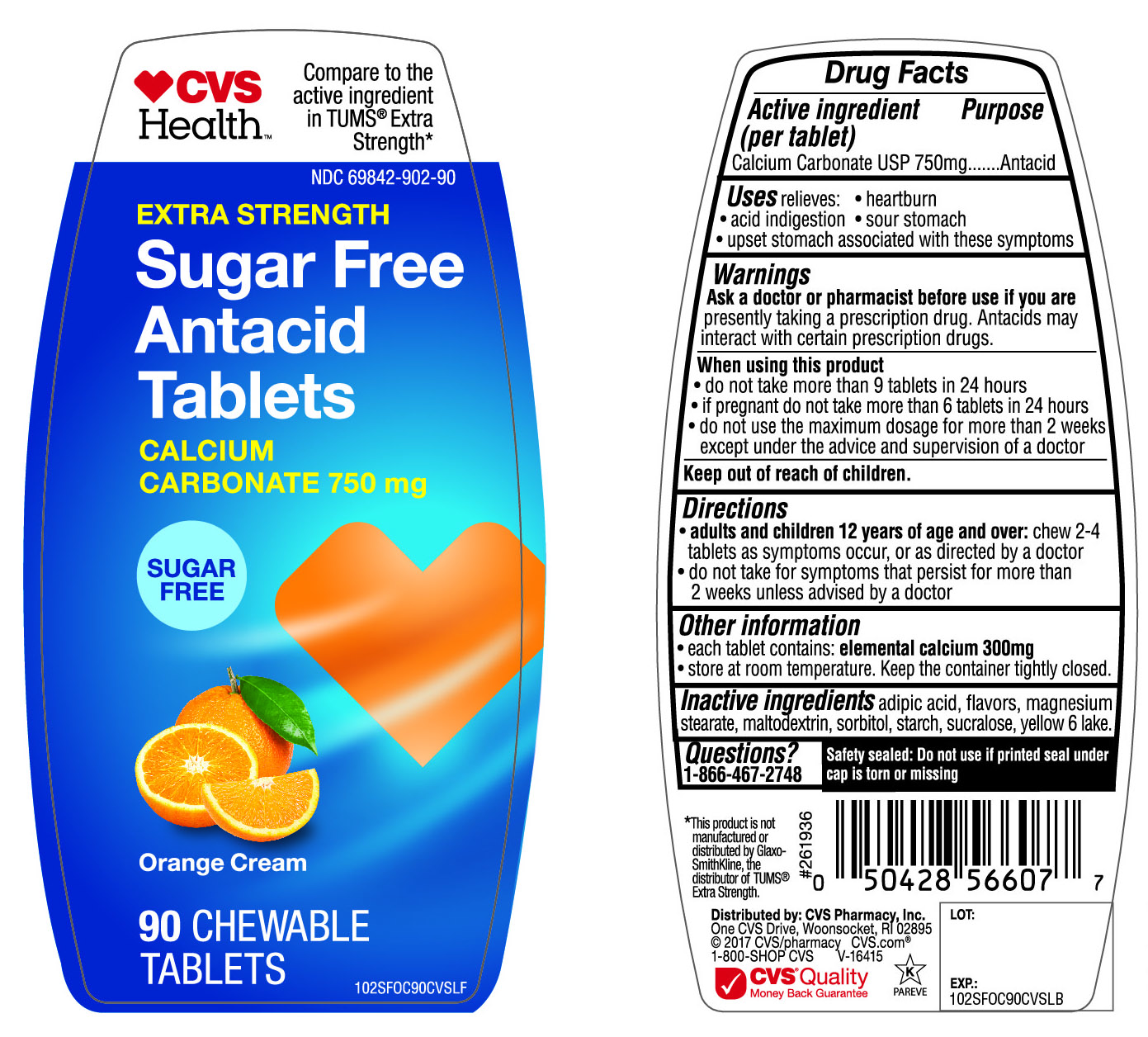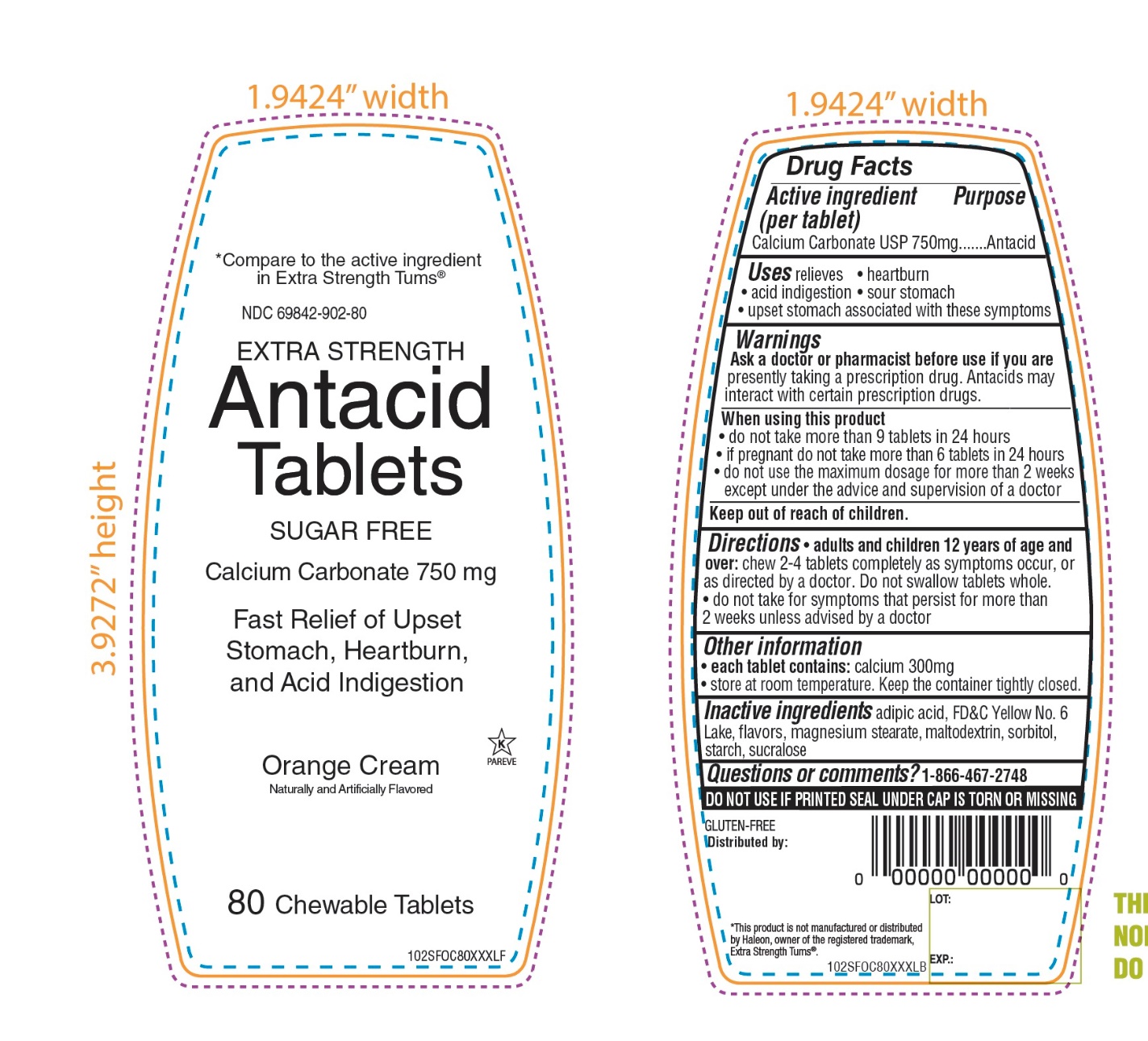 DRUG LABEL: CVS Health Extra Strength Sugar Free Antacid
NDC: 69842-902 | Form: TABLET, CHEWABLE
Manufacturer: CVS Pharmacy,Inc.
Category: otc | Type: HUMAN OTC DRUG LABEL
Date: 20260112

ACTIVE INGREDIENTS: CALCIUM CARBONATE 750 mg/1 1
INACTIVE INGREDIENTS: ADIPIC ACID; MAGNESIUM STEARATE; MALTODEXTRIN; SORBITOL; STARCH, CORN; SUCRALOSE; FD&C YELLOW NO. 6

CVS Health Extra Strength SUGAR FREE Antacid Tablets Calcium Carbonate 750 mg

Active ingredient (per tablet)

Calcium Carbonate USP 750 mg

Purpose

Antacid

Uses

relieves

• heartburn

• acid indigestion

• sour stomach

• upset stomach associated with these symptoms

Warnings

Ask a doctor or pharmacist before use if you are presently taking a prescription drug. Antacids may interact with certain prescription drugs.

When using this product

- do not take more than 9 tablets in 24 hours
- If pregnant do not take more than 6 tablets in 24 hours
- do not use the maximum dosage for more than 2 weeks except under the advice and supervision of a doctor

Directions

- adults and children 12 years of age and over: chew 2-4 tablets as symptoms occur ,or as directed by a doctor
- do not take for symptoms that persist for more than 2 weeks unless advised by a doctor

Other Information

• each tablet contains: elemental calcium 300 mg

• store at room temperature. Keep the container tightly closed.

Inactive ingredients

adipic acid, flavors, magnesium stearate, maltodextrin, sorbitol, starch, sucralose, yellow 6 lake.

Questions?

1-866-467-2748

Safety sealed: Do not use if printed seal under cap is torn or missing

Package/Label Principal Display Panel

NDC 69842-902-90

CVS Health™

Compare to the active ingredient in Tums® Extra Strength *

Extra Strength

Sugar Free

Antacid

Tablets

Calcium Carbonate 750 mg

Sugar Free

Orange Cream

90 CHEWABLE TABLETS

Distributed by: CVS Pharmacy, Inc.

One CVS Drive, Woonsocket, RI 02895

©2017 CVS/Pharmacy CVS .com®

1-800-SHOP CVS

V-16415

CVS Quality

Money Back Guarantee

K PAREVE

*This product is not manufactured or distributed by GlaxoSmithKline, the distributor of TUMS® Extra Strength .